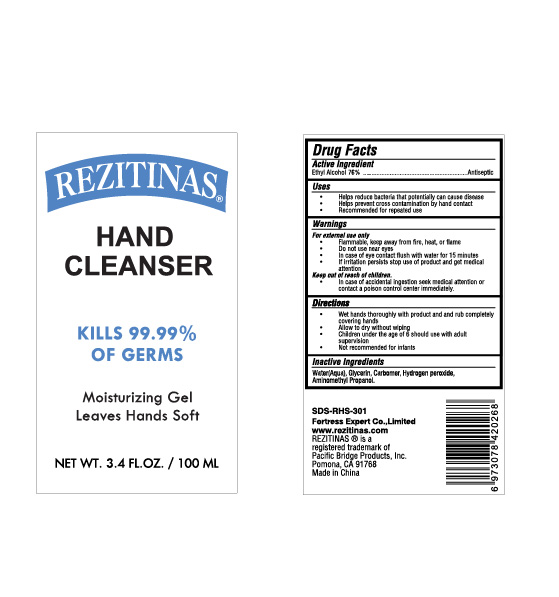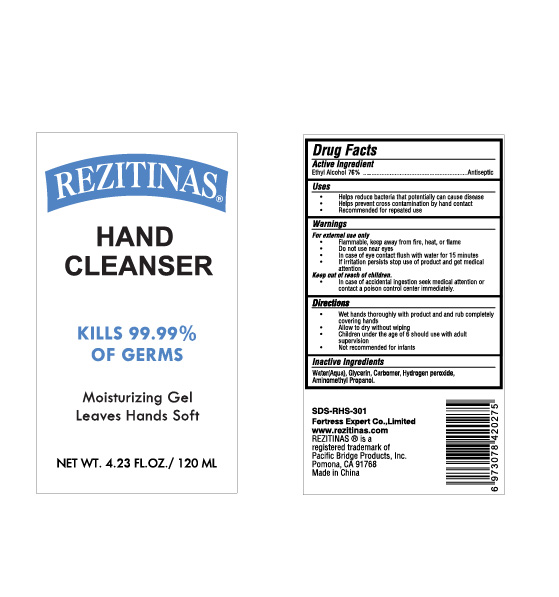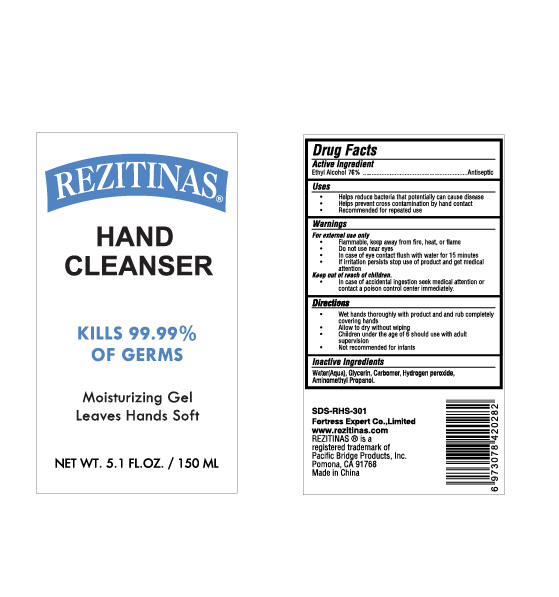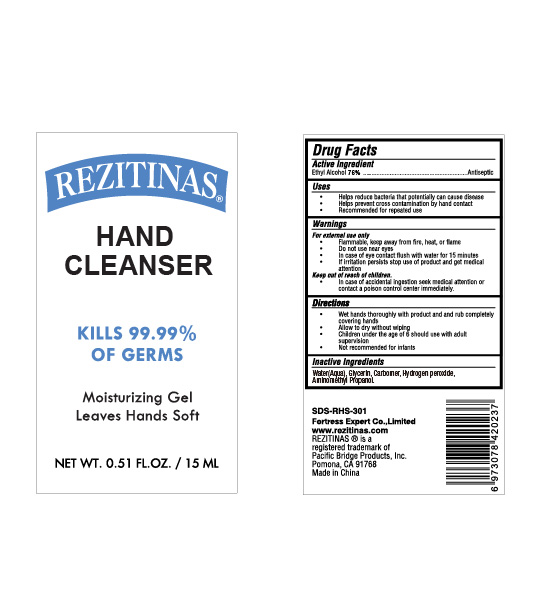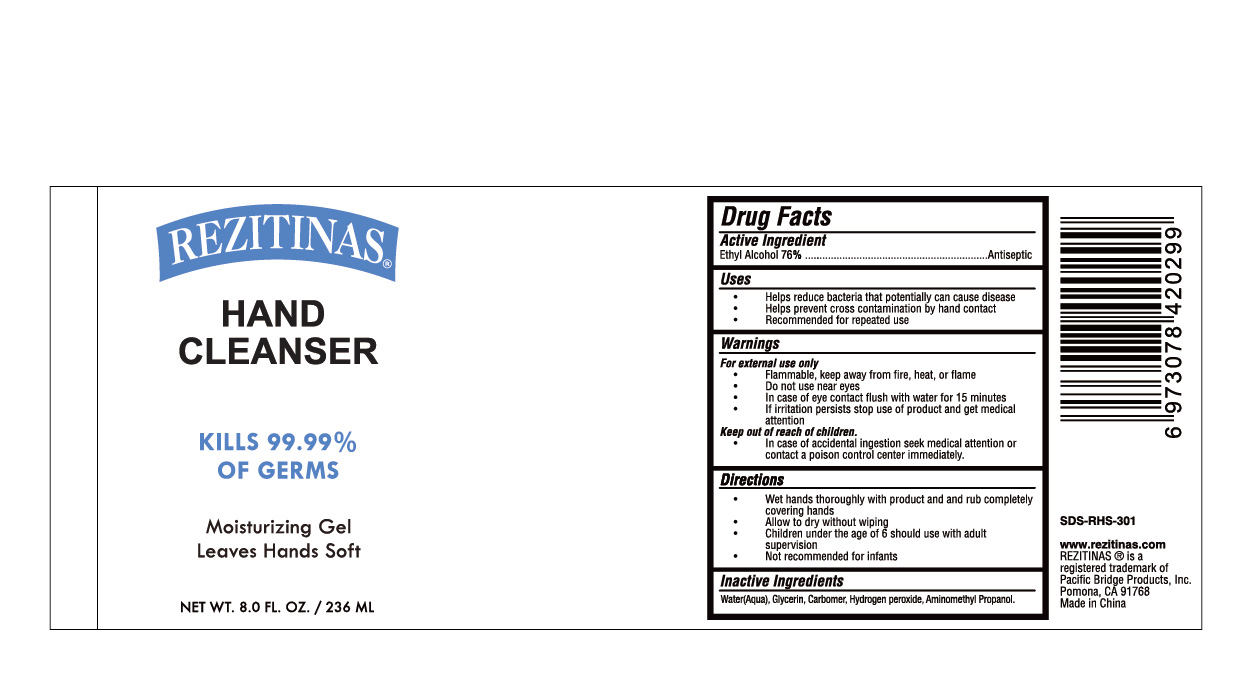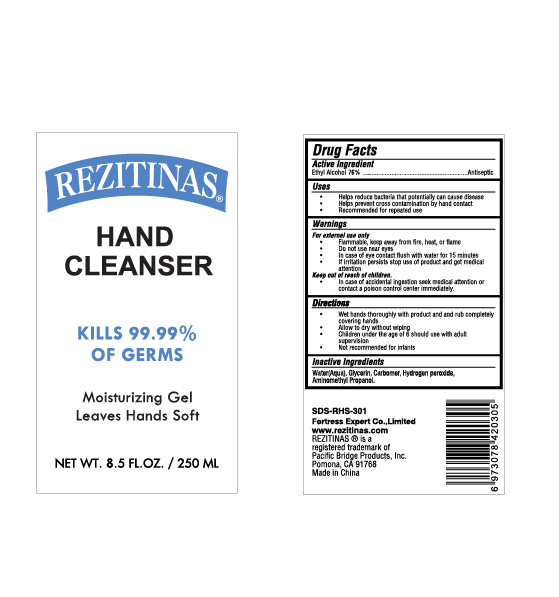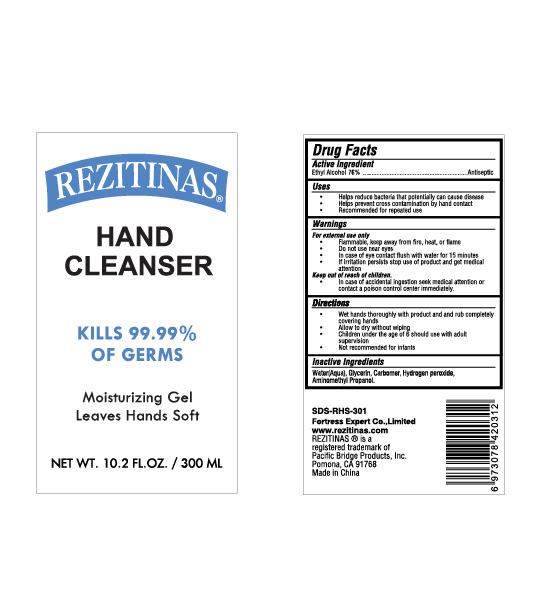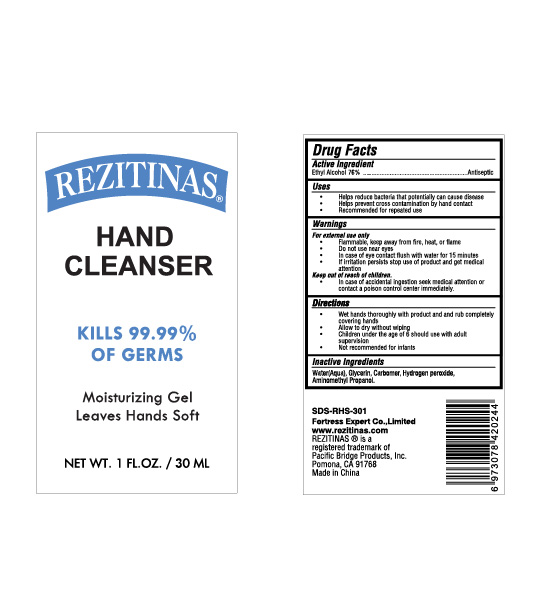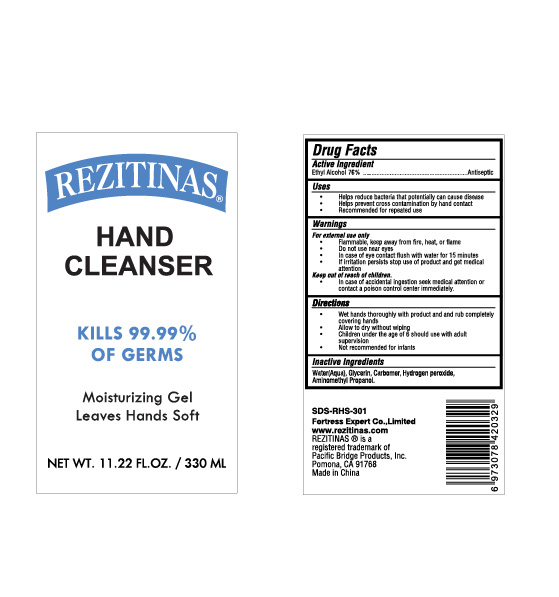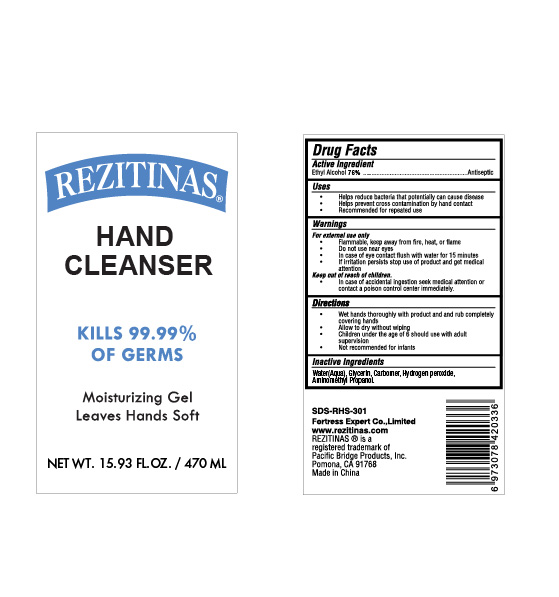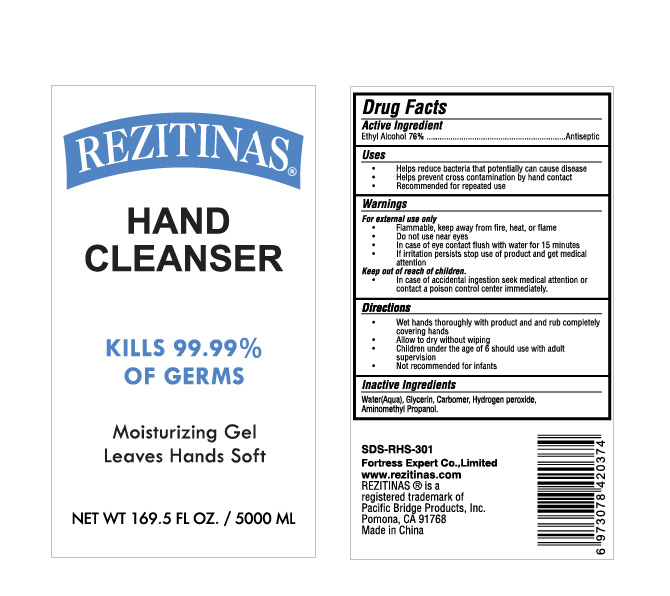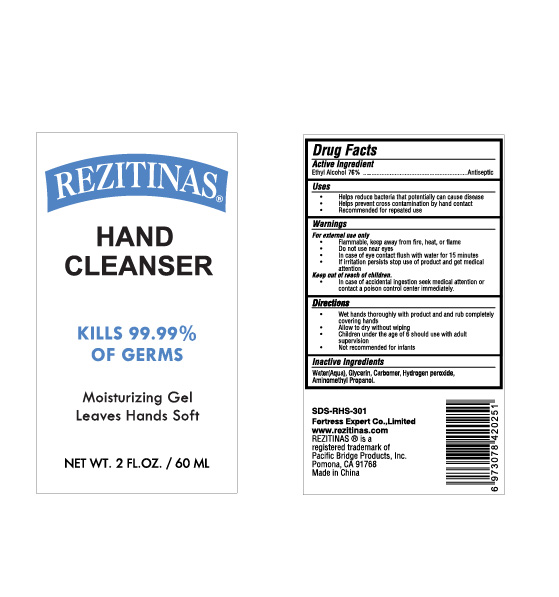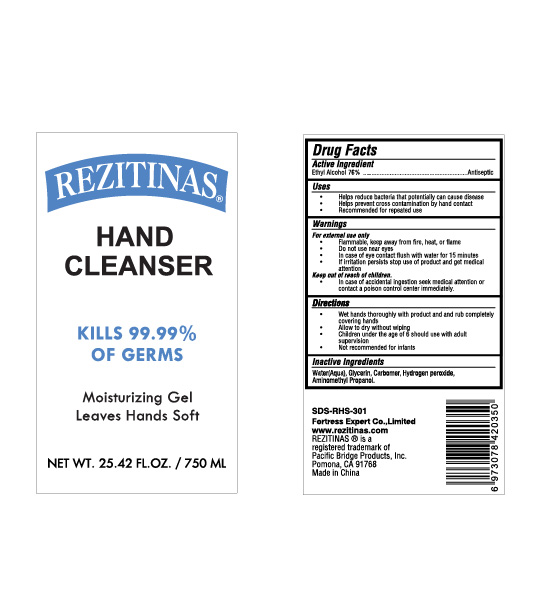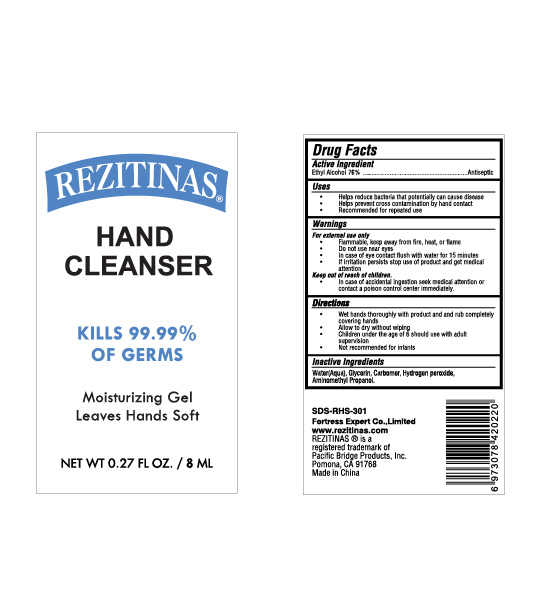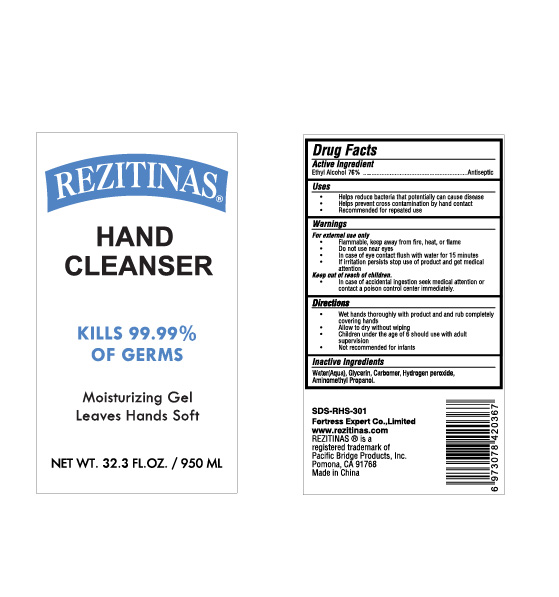 DRUG LABEL: Hand Cleanser
NDC: 73549-003 | Form: GEL
Manufacturer: Fortress Expert Co., Ltd
Category: otc | Type: HUMAN OTC DRUG LABEL
Date: 20200514

ACTIVE INGREDIENTS: ALCOHOL 76 mL/100 mL
INACTIVE INGREDIENTS: AMINOMETHYLPROPANOL; GLYCERIN; WATER; CARBOMER HOMOPOLYMER, UNSPECIFIED TYPE; HYDROGEN PEROXIDE

HAND SANITIZER

Active Ingredient

Ethyl Alcohol 75.05%

Purpose

Antiseptic

Uses

Helps reduce bacteria that potentially can cause disease

Helps prevent cross contamination by hand contact

Recommended for repeated use

Warnings

For external use only

Flammable, keep away from fire, heat,or flame

Do not use near eyes

In case of eye contact flush with water for 15 minutes

if irritation persists stop use of product and get medical attention

Keep out of reach of children.

In case of accidental ingestion seek medical attention or contact a poison control center immediately.

Directions

Wet hands thoroughly with product and and rub completely covering hands

Allow to dry without wiping

Children under the age of 6 should use with adult

supervision

Not recommended for infants

Inactive Ingredients

Walen , Glycerin, Carbomer, Hydrogen peroxideAminomethyl Propanol